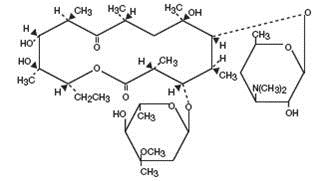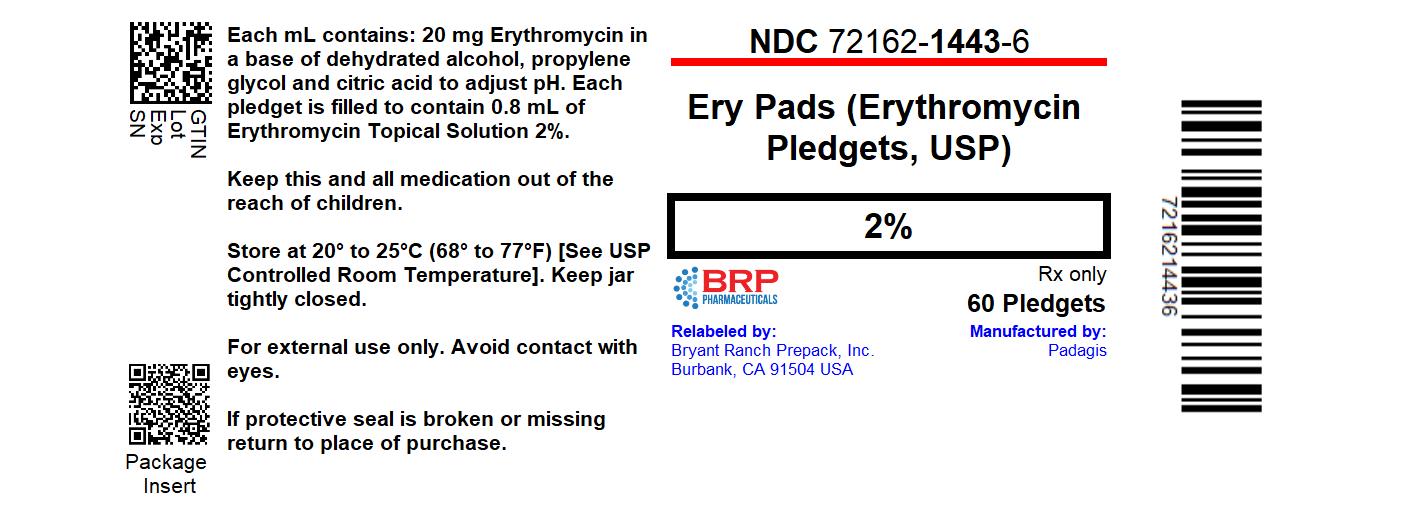 DRUG LABEL: Ery
NDC: 72162-1443 | Form: SWAB
Manufacturer: Bryant Ranch Prepack
Category: prescription | Type: HUMAN PRESCRIPTION DRUG LABEL
Date: 20241224

ACTIVE INGREDIENTS: ERYTHROMYCIN 20 mg/1 mL
INACTIVE INGREDIENTS: ALCOHOL; PROPYLENE GLYCOL; CITRIC ACID MONOHYDRATE

Ery 2% Pads
(Erythromycin Pledgets USP, 2%)

Rx Only

For Dermatologic Use Only

Not for Ophthalmic Use

DESCRIPTION

Ery 2% Pads contain erythromycin, USP for topical dermatologic use. Erythromycin is a macrolide antibiotic produced from a strain of Saccaropolyspora erythraea (formerly Streptomyces erythreus). It is a base and readily forms salts with acids.

Chemically, erythromycin is C37H67NO13. It has the following structural formula:

The chemical name for erythromycin is (3R*,4S*,5S*,6R*,7R*,9R*,11R*,12R*,13S*,14R*)-4-[(2,6-Dideoxy-3-C-methyl-3-O-methyl-α-L-ribo-hexopyranosyl)oxy]-14-ethyl-7,12,13-trihydroxy-3,5,7,9,11,13-hexamethyl-6-[[3,4,6-trideoxy-3-(dimethylamino)-β-D-xylo-hexopyranosyl]oxy] oxacyclotetradecane-2,10-dione.

Erythromycin has the molecular weight of 733.94. It is a white or slightly yellow, crystalline powder, slightly soluble in water, soluble in alcohol, in chloroform, and in ether. It is odorless or practically odorless. It has a pH range between 8.0 and 10.5 in a methanol and water solution prepared by diluting 1 volume of a methanol solution, containing 40 mg per mL, with 19 volumes of water.

Each mL of expressible liquid contains 20 mg erythromycin in a base of dehydrated alcohol, propylene glycol and citric acid to adjust pH. Each pledget is filled to contain 0.8 mL of Erythromycin Topical Solution 2%.

CLINICAL PHARMACOLOGY

The exact mechanism by which erythromycin reduces lesions of acne vulgaris is not fully known; however, the effect appears to be due in part to the antibacterial activity of the drug.

MICROBIOLOGY

Erythromycin acts by inhibition of protein synthesis in susceptible organisms by reversibly binding to 50S ribosomal subunits, thereby inhibiting translocation of aminoacyl transfer-RNA and inhibiting polypeptide synthesis. Antagonism has been demonstrated in vitro between erythromycin, lincomycin, chloramphenicol, and clindamycin.

INDICATIONS AND USAGE

Ery 2% Pads are indicated for the topical treatment of acne vulgaris.

CONTRAINDICATIONS

Ery 2% Pads are contraindicated in those individuals who have shown hypersensitivity to any of its components.

WARNINGS

Pseudomembranous colitis has been reported with nearly all antibacterial agents, including erythromycin, and may range in severity from mild to life-threatening. Therefore, it is important to consider this diagnosis in patients who present with diarrhea subsequent to the administration of antibacterial agents.

Treatment with antibacterial agents alters the normal flora of the colon and may permit overgrowth of clostridia. Studies indicate that a toxin produced by Clostridium difficile is one primary cause of “antibiotic-associated colitis”.

After the diagnosis of pseudomembranous colitis has been established, therapeutic measures should be initiated. Mild cases of pseudomembranous colitis usually respond to drug discontinuation alone. In moderate to severe cases, consideration should be given to management with fluids and electrolytes, protein supplementation and treatment with an antibacterial drug clinically effective against C. difficile colitis.

PRECAUTIONS

General -

For topical use only; not for ophthalmic use. Concomitant topical acne therapy should be used with caution because a possible cumulative irritancy effect may occur, especially with the use of peeling, desquamating, or abrasive agents.

The use of antibiotic agents may be associated with the overgrowth of antibiotic-resistant organisms. If this occurs, discontinue use and take appropriate measures.

Avoid contact with eyes and all mucous membranes.

Information for Patients -

Patients using Ery 2% Pads should receive the following information and instructions:

1. This medication is to be used as directed by the physician. It is for external use only. Avoid contact with the eyes, nose, mouth, and all mucous membranes.

2. This medication should not be used for any disorder other than that for which it was prescribed.

3. Patients should not use any other topical acne medication unless otherwise directed by their physician.

4. Patients should report to their physician any signs of local adverse reactions.

Carcinogenesis, Mutagenesis, Impairment of Fertility -

No animal studies have been performed to evaluate the carcinogenic and mutagenic potential or effects on fertility of topical erythromycin. However, long-term (2-year) oral studies in rats with erythromycin ethylsuccinate and erythromycin base did not provide evidence of tumorigenicity. There was no apparent effect on male or female fertility in rats fed erythromycin (base) at levels up to 0.25% of diet.

Pregnancy: Teratogenic Effects: Pregnancy Category B -

There was no evidence of teratogenicity or any other adverse effect on reproduction in female rats fed erythromycin base (up to 0.25% diet) prior to and during mating, during gestation and through weaning of two successive litters.

There are, however, no adequate and well-controlled studies in pregnant women. Because animal reproduction studies are not always predictive of human response, this drug should be used in pregnancy only if clearly needed. Erythromycin has been reported to cross the placental barrier in humans, but fetal plasma levels are generally low.

Nursing Women -

It is not known whether erythromycin is excreted in human milk after topical application. However, erythromycin is excreted in human milk following oral and parenteral erythromycin administration. Therefore, caution should be exercised when erythromycin is administered to a nursing woman.

Pediatric Use -

Safety and effectiveness of this product in pediatric patients have not been established.

ADVERSE REACTIONS

The following local adverse reactions have been reported occasionally: peeling, dryness, itching, erythema, and oiliness. Irritation of the eyes and tenderness of the skin have also been reported with topical use of erythromycin. Generalized urticarial reactions, possibly related to the use of erythromycin, which required systemic steroid therapy have been reported.

DOSAGE AND ADMINISTRATION

The Ery 2% Pads should be rubbed over the affected area twice a day (morning and evening) after skin is thoroughly washed with warm water and soap and patted dry. Acne lesions on the face, neck, shoulders, chest, and back may be treated in this manner. Additional pledgets may be used, if needed. Each pledget should be used once and discarded. Wash hands after application. Close jar tightly after each use. Drying and peeling may be controlled by reducing the frequency of applications.

HOW SUPPLIED

Ery 2% Pads are available as follows:

- A plastic jar containing 60 pledgets (NDC 72162-1443-6)

Each pledget is filled to contain 0.8 mL of Erythromycin Topical Solution 2%.

Repackaged/Relabeled by:
Bryant Ranch Prepack, Inc.
Burbank, CA 91504

STORAGE

Keep jar tightly closed.

Store at 20-25°C (68-77°F) [see USP Controlled Room Temperature].

Manufactured by Padagis, Yeruham, Israel

Distributed By Padagis, Allegan, MI 49010
www.padagis.com

Rev. 02-22

6E500 RC J5

PACKAGE LABEL

Erythromycin 2% Pads